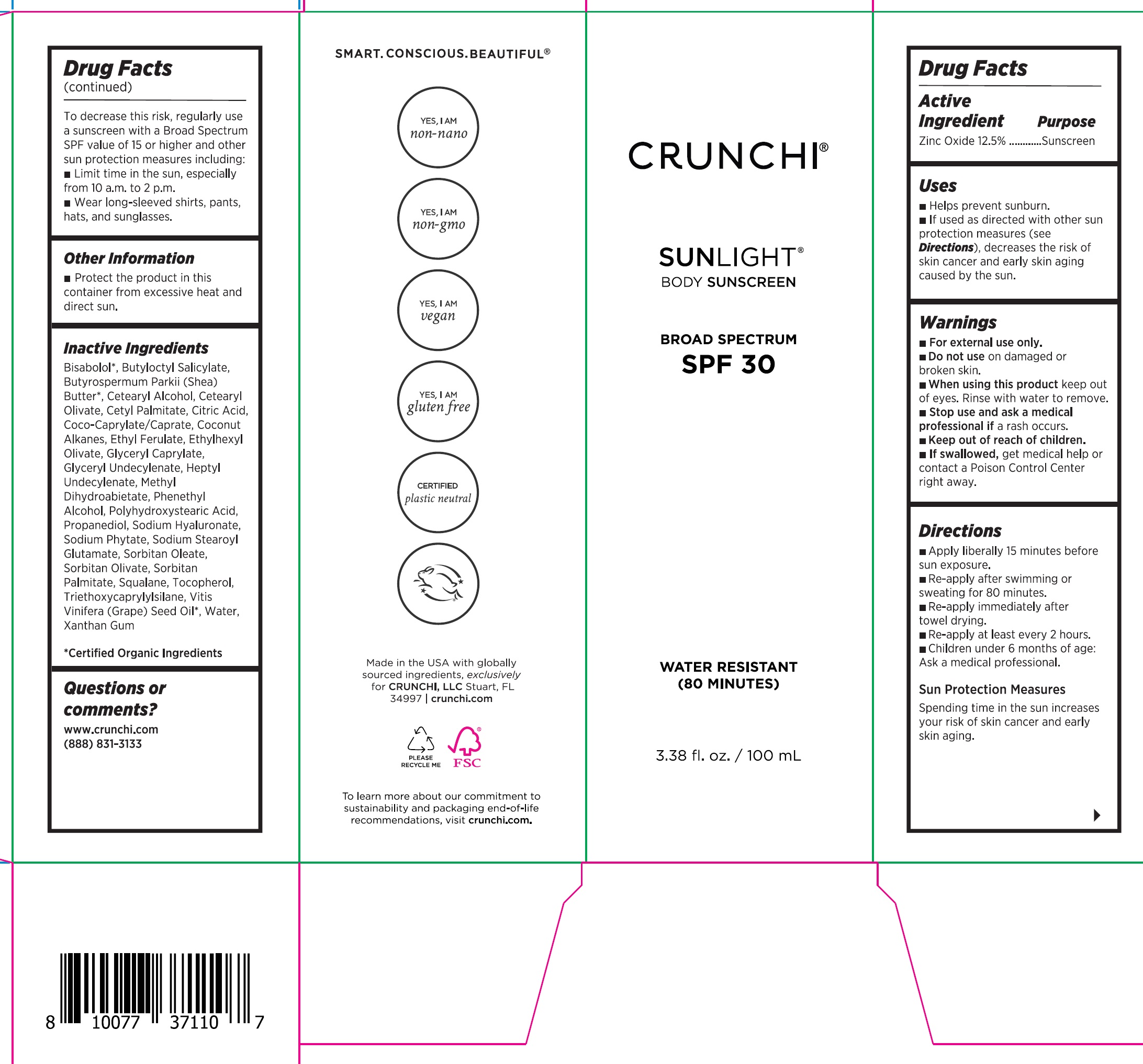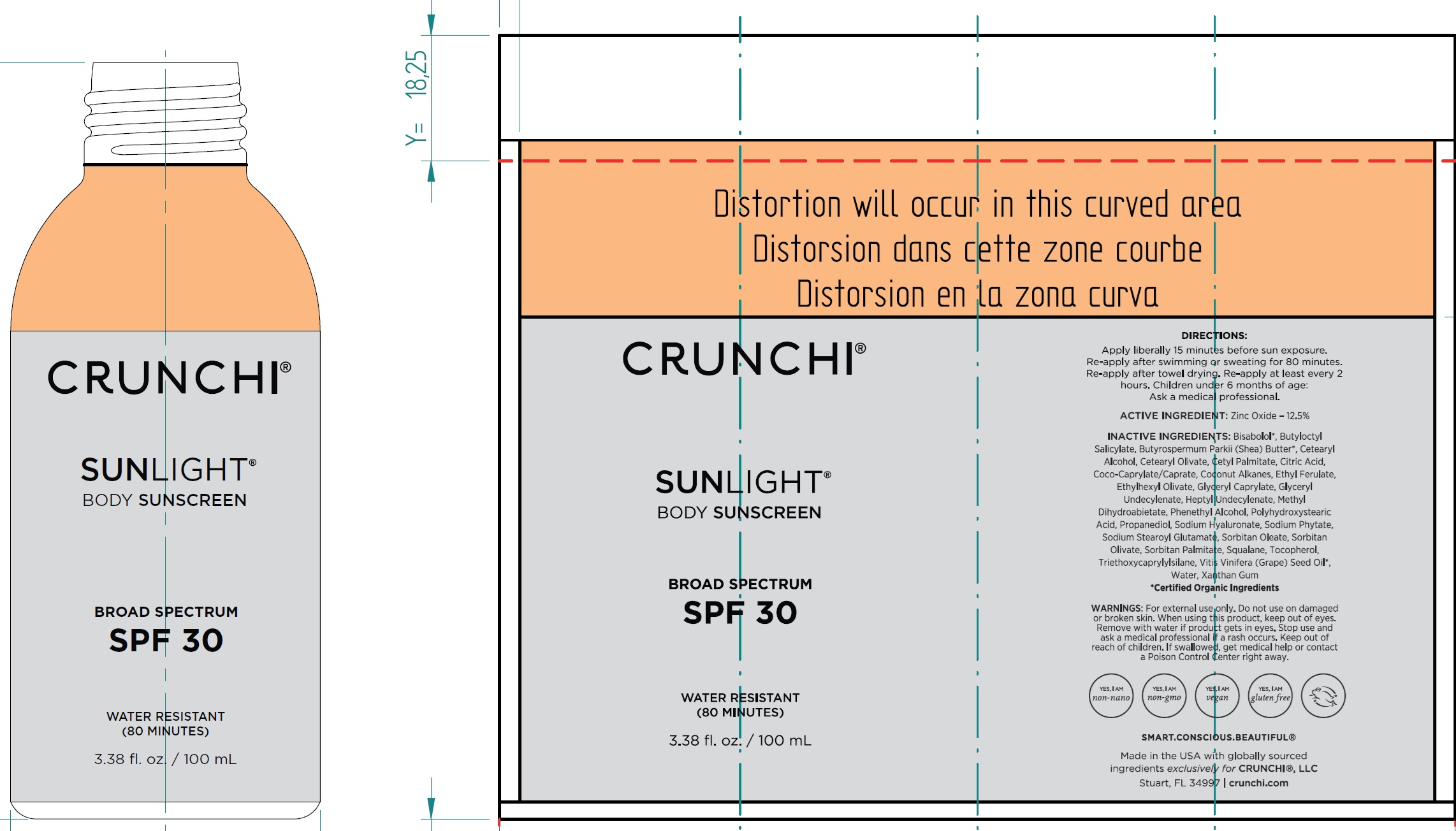 DRUG LABEL: Crunchi Sunlight Body Sunscreen SPF 30
NDC: 72444-0201 | Form: LIQUID
Manufacturer: Crunchi, LLC.
Category: otc | Type: HUMAN OTC DRUG LABEL
Date: 20251215

ACTIVE INGREDIENTS: ZINC OXIDE 125 mg/1 mL
INACTIVE INGREDIENTS: LEVOMENOL; BUTYLOCTYL SALICYLATE; SHEA BUTTER; CETOSTEARYL ALCOHOL; CETEARYL OLIVATE; CETYL PALMITATE; CITRIC ACID MONOHYDRATE; COCOYL CAPRYLOCAPRATE; COCONUT ALKANES; ETHYL FERULATE; ETHYLHEXYL OLIVATE; GLYCERYL CAPRYLATE; HEPTYL UNDECYLENATE; METHYL DIHYDROABIETATE; PHENYLETHYL ALCOHOL; PROPANEDIOL; HYALURONATE SODIUM; PHYTATE SODIUM; SODIUM STEAROYL GLUTAMATE; SORBITAN MONOOLEATE; SORBITAN OLIVATE; SORBITAN MONOPALMITATE; SQUALANE; TOCOPHEROL; TRIETHOXYCAPRYLYLSILANE; GRAPE SEED OIL; WATER; XANTHAN GUM

Crunchi Sunlight Body Sunscreen SPF 30

Active Ingredient

Zinc Oxide 12.5%

Purpose

Sunscreen

Uses

- Helps prevent sunburn.
- If used as directed with other sun protection measures (see Directions), decreases the risk of skin cancer and early skin aging caused by the sun.

Warnings

- For external use only.

• Do not use

on damaged or broken skin.

• When using this product

keep out of eyes. Rinse with water to remove.

• Stop use and ask a medical professional if

a rash occurs.

• Keep out of reach of children.

- If swallowed,get medical help or contact a Poison Control Center right away.

Directions

- Apply liberally 15 minutes before sun exposure.
- Re-apply after swimming or sweating for 80 minutes.
- Re-apply immediately after towel drying.
- Re-apply at least every 2 hours.
- Children under 6 months of age: Ask a medical professional.

Sun Protection MeasuresSpending time in the sun increases your risk of skin cancer and early skin aging. To decrease the risk, regularly use a sunscreen with a Broad Spectrum SPF value of 15 or higher and other sun protection measures including:

- Limit time in the sun, especially from 10 a.m. to 2 p.m.
- Wear long-sleeved shirts, pants, hats, and sunglasses.

Other Information

- Protect the product in this container from excessive heat and direct sun.

Inactive Ingredients

Bisabolol*, Butyloctyl Salicylate, Butyrospermum Parkii (Shea) Butter*, Cetearyl Alcohol, Cetearyl Olivate, Cetyl Palmitate, Citric Acid, Coco Caprylate/Caprate, Coconut Alkanes, Ethyl Ferulate, Ethylhexyl Olivate, Glyceryl Caprylate, Glyceryl Undecylenate, Heptyl Undecylenate, Methyl Dihydroabietate, Phenethyl Alcohol, Polyhydroxystearic Acid, Propanediol, Sodium Hyaluronate, Sodium Phytate, Sodium Stearoyl Glutamate, Sorbitan Oleate, Sorbitan Olivate, Sorbitan Palmitate, Squalane, Tocopherol, Triethoxycaprylylsilane, Vitis Vinifera (Grape) Seed Oil*, Water, Xanthan Gum

*Certified Organic Ingredients

Questions or comments?

www.crunchi.com (888) 831-3133